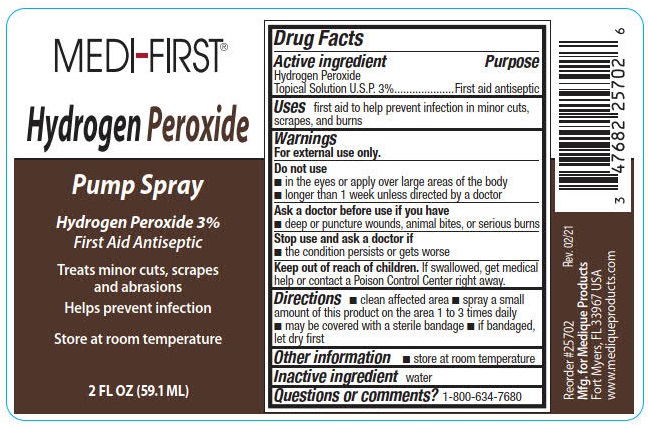 DRUG LABEL: Medi-First Hydrogen Peroxide
NDC: 47682-259 | Form: SPRAY
Manufacturer: Unifirst First Aid Corporation
Category: otc | Type: HUMAN OTC DRUG LABEL
Date: 20240117

ACTIVE INGREDIENTS: HYDROGEN PEROXIDE 43.275 g/1 L
INACTIVE INGREDIENTS: WATER

Medi-First Hydrogen Peroxide Spray

Drug Facts

Active ingredient

Hydrogen Peroxide Topical Solution U.S.P. 3%

Purpose

First aid antiseptic

Uses

first aid to help prevent infection in minor cuts, scrapes, and burns

Warnings

For external use only.

Do not use

- in the eyes or apply over large areas of the body
- longer than 1 week unless directed by a doctor

Ask a doctor before use if you have

- deep or puncture wounds, aniamal bites, or serious burns

Stop use and ask a doctor if

- the condition persistes or gets worse

Keep out of reach of children.

If swallowed, get medical help or contact a Poison Control Center right away.

Directions

- clean affected area
- spray a small amount of this product on the area 1 to 3 times daily
- may be covered with a sterile bandage
- if bandaged, let dry first

Other information

- store at room temperature

Inactive ingredient water

Questions or comments? 1-800-634-7680

PACKAGE LABEL

Medi-First®

Hydrogen Peroxide

Pump Spray

Hydrogen Peroxide 3%

First Aid Antiseptic

Treats minor cuts, scrapes and abrasions

Helps prevent infection

Store at room temperature

2 FL OZ (59.1 ML)